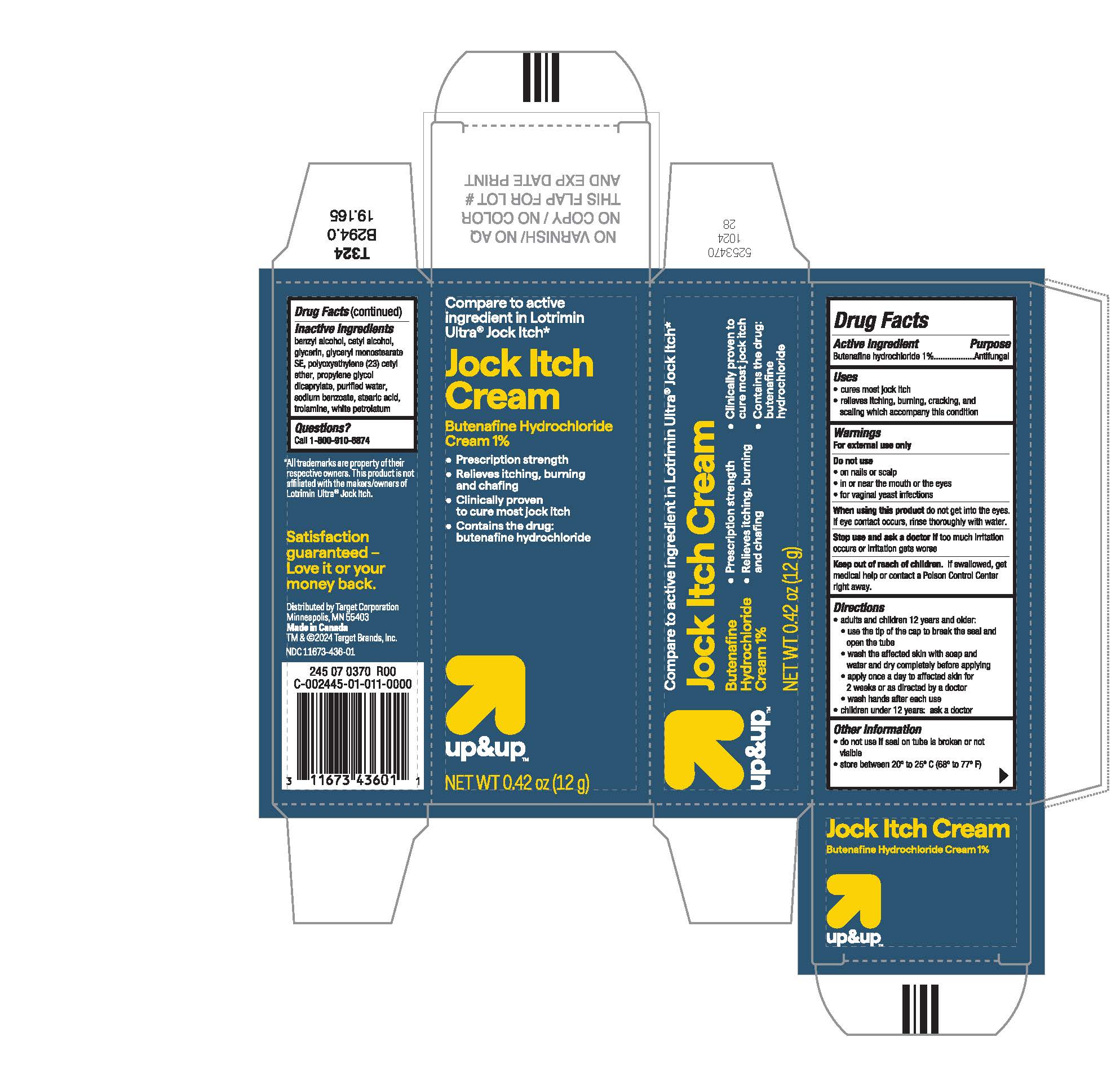 DRUG LABEL: Jock Itch Cream
NDC: 11673-436 | Form: CREAM
Manufacturer: TARGET CORPORATION
Category: otc | Type: HUMAN OTC DRUG LABEL
Date: 20250703

ACTIVE INGREDIENTS: BUTENAFINE HYDROCHLORIDE 10 mg/1 g
INACTIVE INGREDIENTS: CETYL ALCOHOL; GLYCERIN; CETETH-23; WHITE PETROLATUM; SODIUM BENZOATE; TROLAMINE; PROPYLENE GLYCOL DICAPRYLATE; GLYCERYL STEARATE SE; BENZYL ALCOHOL; STEARIC ACID; WATER

Target Butenafine HCl Cream 1%- 12 g

Drug Facts

ACTIVE INGREDIENT

Butenafine Hydrochloride 1%

PURPOSE

Antifungal

Uses

- cures most jock itch
- relieves itching, burning, crackling, and scaling which accompany this condition

Warnings

For external use only

Do not use

- on nails or scalp
- in or near the mouth or the eyes
- for vaginal yeast infections

WHEN USING

When using this productdo not get into the eyes. If eye contact occurs, rinse thoroughly with water.

Stop use and ask a doctor iftoo much irritation occurs or irration gets worse.

Keep out of reach of children.If swallowed, get medical help or contact a Poision Control Center right away.

Directions

- adults and children 12 years and older:

- use the tip of the cap to break the seal and open the tube
- wash the affected skin with soap and water and dry completely before applying
- apply once a day to affected skin for 2 weeks or as directed by a doctor
  - wash hands after each use

- children under 12 years: ask a doctor

Other Information

- do not use if seal on tube is broken or not visible
- store between 20° to 25° C (68° to 77° F)

INACTIVE INGREDIENT

Benzyl Alcohol, Cetyl Alcohol, Glycerin, Glyceryl Monostearate SE, Polyoxyethylene (23) Cetyl Ether, Propylene Glycol Dicaprylate, Purified Water, Sodium Benzoate, Stearic Acid, Trolamine, White Petrolatum.

Question?

1-800-910-6874

DISTRIBUTED BY:

Target Corporation.,

Minneapolis, MN 55403

PRINCIPAL DISPLAY PANEL - 12 g Tube Carton

Compare to active ingredient in Lotrimin Ultra®Jock Itch*

Jock Itch

Cream

Butenafine Hydrochloride

Cream 1%

- Prescription strength
- Relieves itching, burning and chafing
- Clinically proven to cure most jock itch
- Contains the drug:

butenafine hydrochloride

up&upTM

NET WT 0.42 oz (12 g)